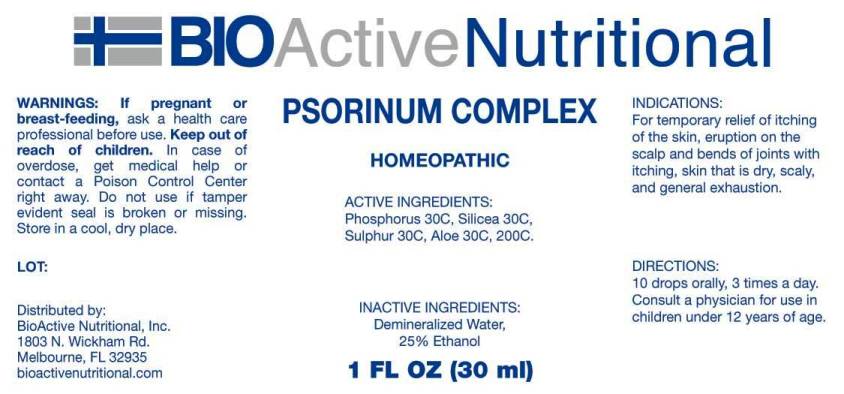 DRUG LABEL: Psorinum Complex
NDC: 43857-0262 | Form: LIQUID
Manufacturer: BioActive Nutritional, Inc.
Category: homeopathic | Type: HUMAN OTC DRUG LABEL
Date: 20161229

ACTIVE INGREDIENTS: PHOSPHORUS 30 [hp_C]/1 mL; SILICON DIOXIDE 30 [hp_C]/1 mL; SULFUR 30 [hp_C]/1 mL; ALOE 30 [hp_C]/1 mL
INACTIVE INGREDIENTS: WATER; ALCOHOL

DRUG FACTS:

ACTIVE INGREDIENTS:

Phosphorus 30C, Silicea 30C, Sulphur 30C, Aloe 30C, 200C.

INDICATIONS:

For temporary relief of itching of the skin, eruption on the scalp and bends of joints with itching, skin that is dry, scaly, and general exhaustion.

WARNINGS:

If pregnant or breast-feeding, ask a health care professional before use.

Keep out of reach of children. In case of overdose, get medical help or contact a Poison Control Center right away.

Do not use if tamper evident seal is broken or missing.

Store in cool, dry place.

Keep out of reach of children. In case of overdose, get medical help or contact a Poison Control Center right away.

DIRECTIONS:

10 drops orally, 3 times a day. Consult a physician for use in children under 12 years of age.

INDICATIONS:

For temporary relief of itching of the skin, eruption on the scalp and bends of joints with itching, skin that is dry, scaly, and general exhaustion.

INACTIVE INGREDIENTS:

Demineralized Water, 25% Ethanol.

QUESTIONS:

Distributed by:
BioActive Nutritional, Inc.
1803 N. Wickham Rd.
Melbourne, FL 32935
bioactivenutritional.com

PACKAGE LABEL DISPLAY

BIOActive Nutritional

PSORINUM COMPLEX

HOMEOPATHIC

1 FL OZ (30 ml)